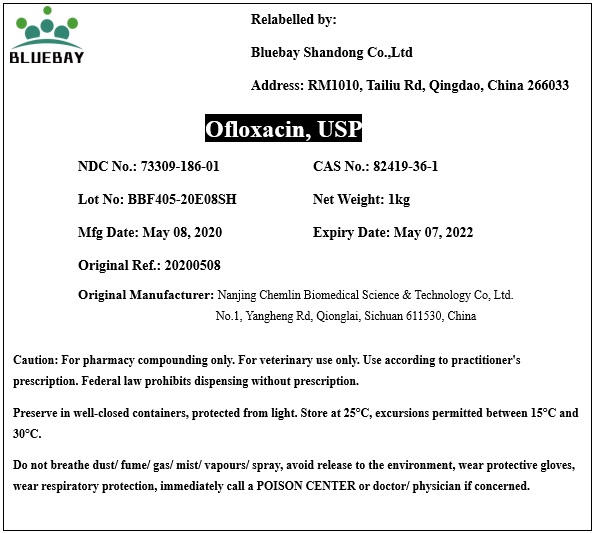 DRUG LABEL: Ofloxacin
NDC: 73309-186 | Form: POWDER
Manufacturer: BLUEBAY SHANDONG CO.,LTD
Category: other | Type: BULK INGREDIENT
Date: 20200904

ACTIVE INGREDIENTS: OFLOXACIN 1 kg/1 kg

Ofloxacin